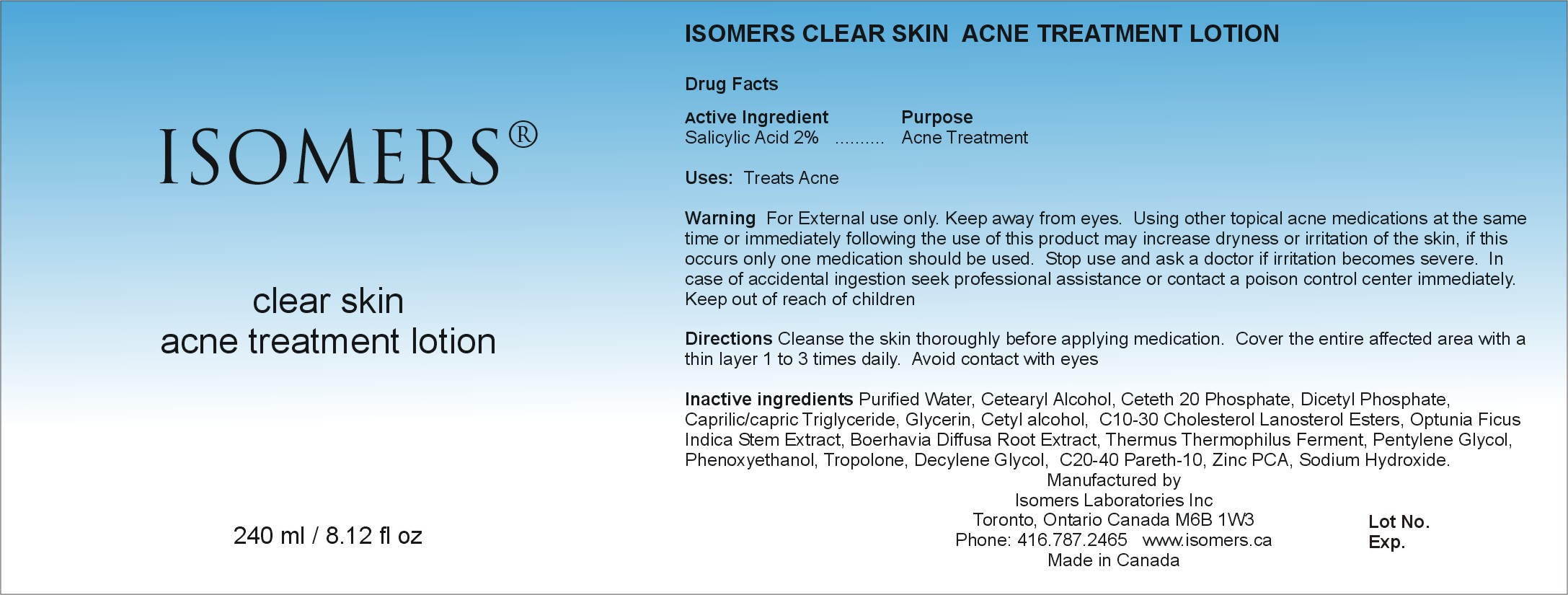 DRUG LABEL: Isomers Clear Skin Acne Treatment Lotion
NDC: 64990-605 | Form: LOTION
Manufacturer: Isomers Laboratories Inc
Category: otc | Type: HUMAN OTC DRUG LABEL
Date: 20100210

ACTIVE INGREDIENTS: SALICYLIC ACID 0.02 mL/1 mL
INACTIVE INGREDIENTS: WATER; CETOSTEARYL ALCOHOL; DIHEXADECYL PHOSPHATE; MEDIUM-CHAIN TRIGLYCERIDES; GLYCERIN; CETYL ALCOHOL; OPUNTIA FICUS-INDICA; PHENOXYETHANOL; SODIUM HYDROXIDE

DRUG FACTS

ACTIVE INGREDIENT

Enter section text here

Active Ingredient:

Salicylic Acid 2%

PURPOSE

Enter section text here

Purpose:

Acne Treatment

ASK DOCTOR

Enter section text here

Stop use and ask doctor

Irritation becomes Severe

KEEP OUT OF REACH OF CHILDREN

Enter section text here

Keep out of reach of children

WARNINGS

Enter section text here

Warnings:

- For external use only
- Keep away from eyes
- Using other topical acne medications at the same time or immediately following the use of this product may increase dryness or irritation of the skin, if this occurs only one medication should be used.
- In case of accidental ingestion seek professional help or contact a poison control center immediately

INACTIVE INGREDIENT

Enter section text here

Inactive ingredients:

Purified water, Cetearyl Alcohol, Ceteth 20 Phosphate, Dicetyl Phosphate, Caprylic/Capric Triglyceride, Glycerin, Cetyl Alcohol, C 10-30 Cholesterol Lanosterol Esters, Optunia Ficus Indica stem Extract, Boerhavia Diffusa Root Extract, Thermus Thermophilus Ferment, Pentylene Glycol, Phenoxyethanol, Tropolone, Decylene Glycol, C 20-40 Pareth 10, Zinc PCA, Sodium Hydroxide.

PACKAGE LABEL

CSATL240.jpg